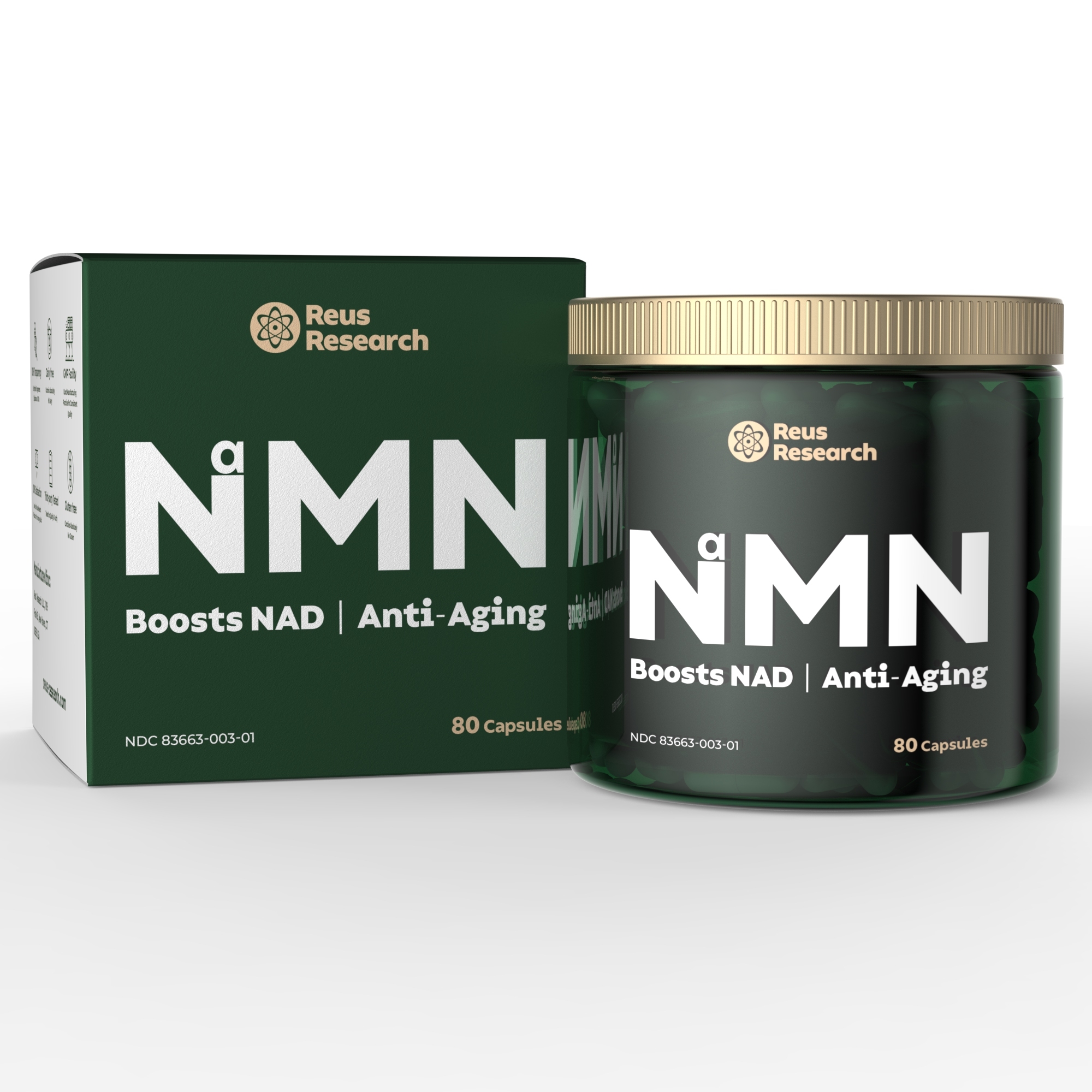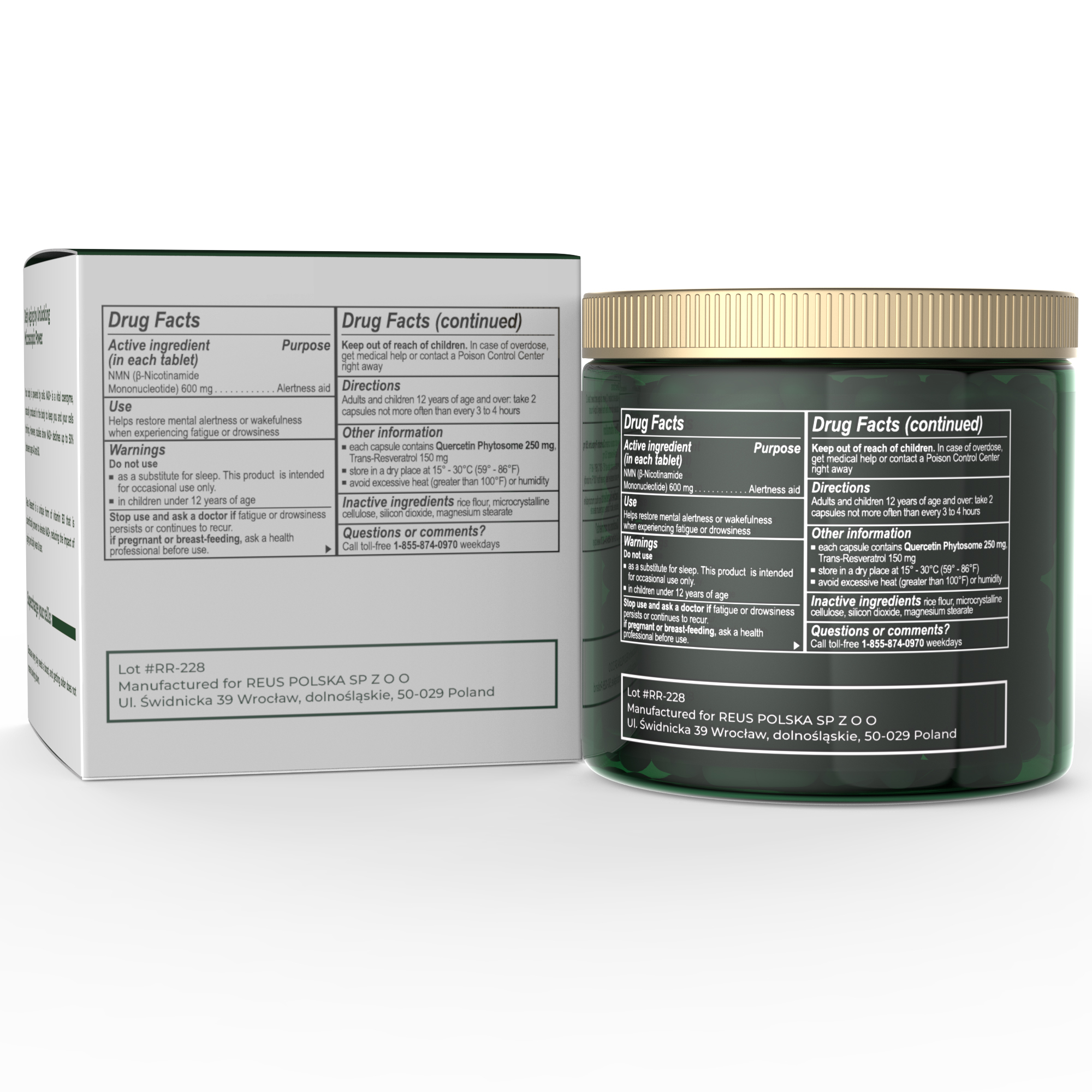 DRUG LABEL: REUS NR
NDC: 83663-003 | Form: CAPSULE
Manufacturer: REUS POLSKA SP Z O O
Category: otc | Type: HUMAN OTC DRUG LABEL
Date: 20230915

ACTIVE INGREDIENTS: NICOTINAMIDE MONONUCLEOTIDE 600 mg/1 1
INACTIVE INGREDIENTS: RESVERATROL 150 mg/1 1

ACTIVE INGREDIENT

NMN (B-Nicotinamide Mononucleotide) 600mg

DO NOT USE

1. as aubstitute for sleep. This product is intended for occastional use only.

2. In children under 12 years of age

INACTIVE INGREDIENT

Rice flour, microcrystalline cellulose, silicon dioxide, magnesium stearate

Keep out of reach of Children.

PREGNANCY OR BREAST FEEDING

If pregrant or breast feeding, ask a health professional before use.

Do Not Use

as substitute for sleep. This product is intended for occasional use only.

QUESTIONS

Call toll-free 1-855-874-0970 weekdays

STORAGE AND HANDLING

Store id a dry place at 15 - 30C (59 - 86F)

Avoid excessive heat (greater than 100F) or humidity

WARNINGS AND PRECAUTIONS

Adults and children 12 years of age and over: take 2 capsules not more often than every 3 to 4 hours

DOSAGE AND ADMINISTRATION

Each capsule contains Quercetin Phytosome 250mb, Trans-Resveratrol 150 mg

INDICATIONS AND USAGE

Adults and children 12 years of age and over: take 2 capsules not more often than every 3 to 4 hours

PURPOSE

Helps restore mental alertness or wakefulness when experiencing fatigue or drowsiness.